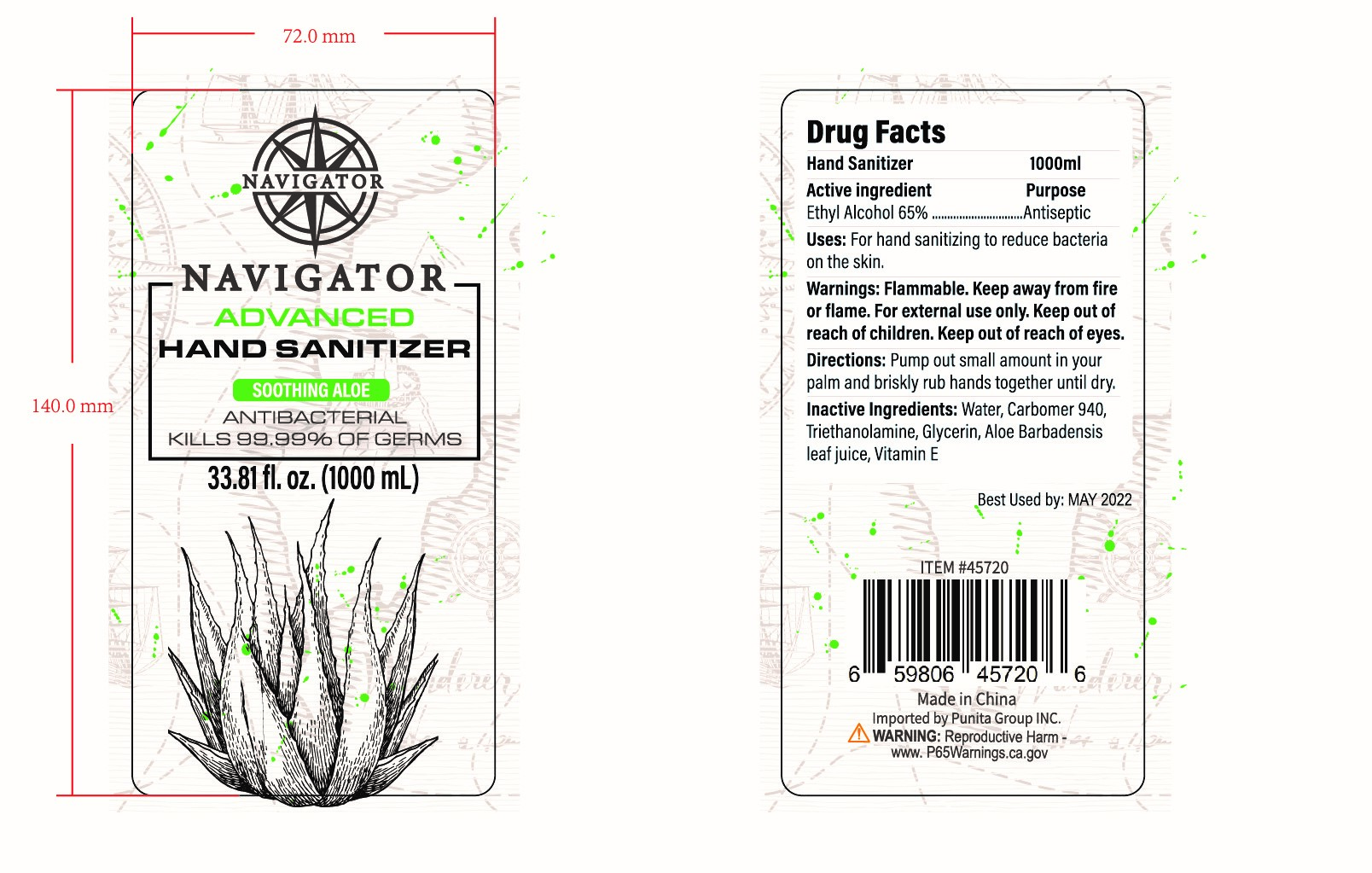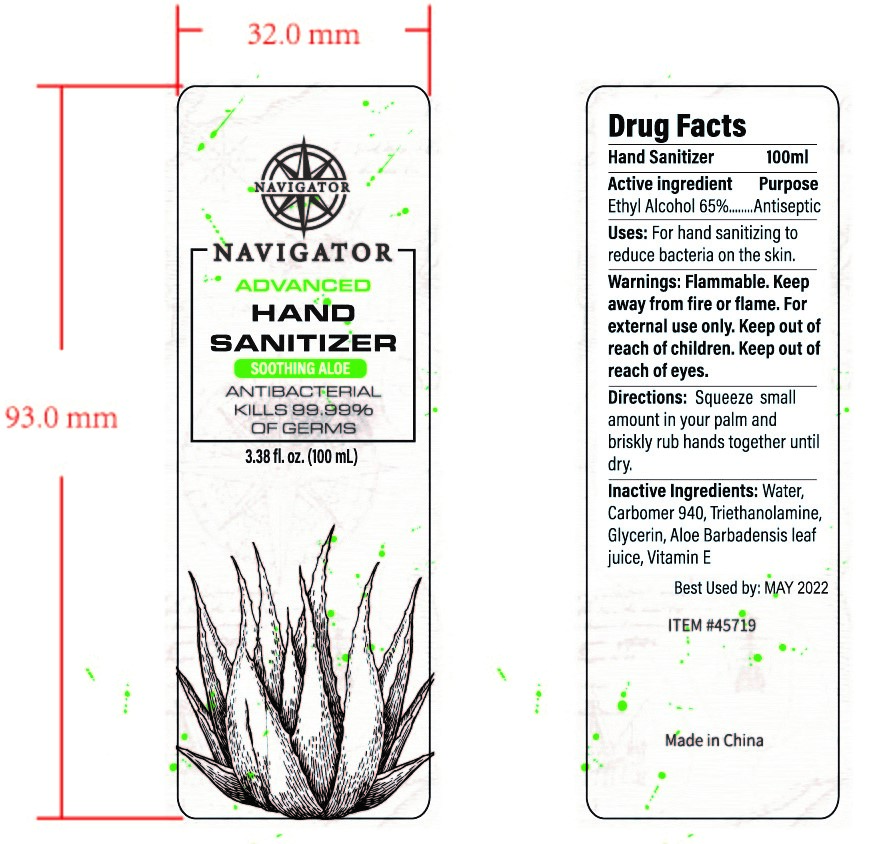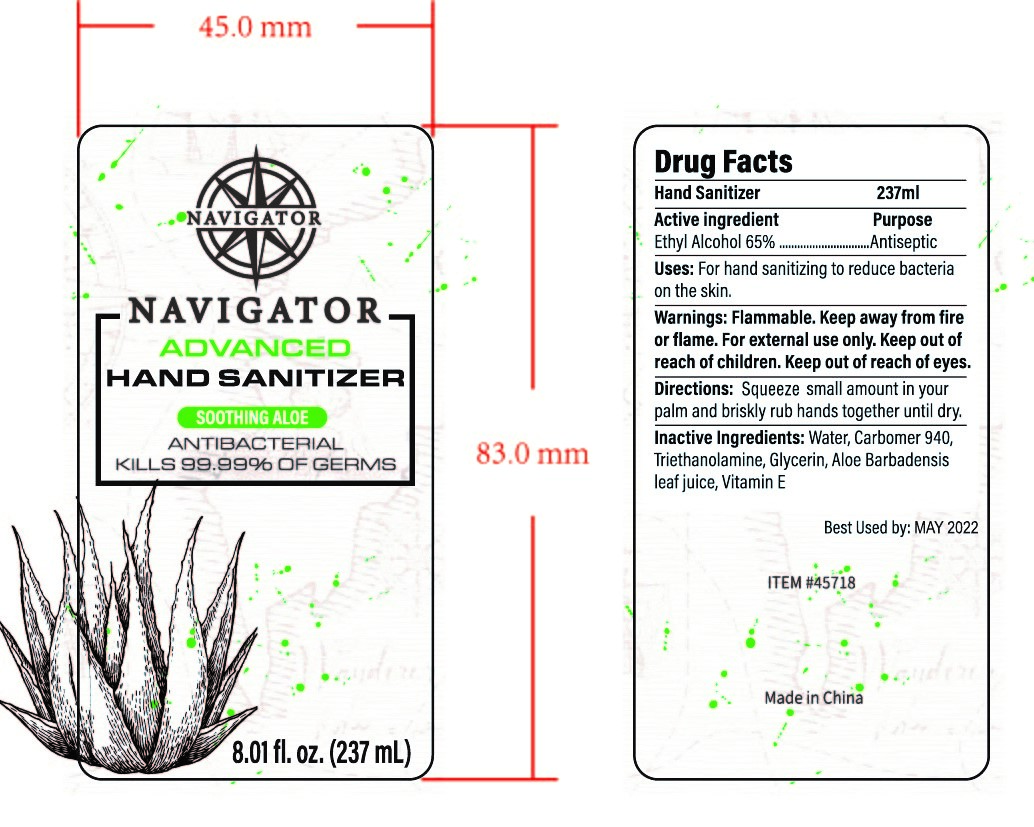 DRUG LABEL: HAND SANITIZER
NDC: 47993-243 | Form: GEL
Manufacturer: NINGBO JIANGBEI OCEAN STAR TRADING CO.,LTD
Category: otc | Type: HUMAN OTC DRUG LABEL
Date: 20201104

ACTIVE INGREDIENTS: ALCOHOL 65 g/112 mL
INACTIVE INGREDIENTS: CARBOMER 940 12 g/112 mL; TRIETHANOLAMINE BENZOATE; WATER; TOCOPHEROL; ALOE VERA LEAF; GLYCERIN 2 g/112 mL

47993-243

Active ingredients

Ethyl Alcohol 65%

PURPOSE

Antiseptic

Warnings:

Flammable. Keep away from fire or flame. For external use only. Keep out of reach of children. Keep out of reach of eyes.

Keep out of reach of children.

Uses：

For hand sanitizing to readuce bacteria on the skin.

Directions:

Squeeze small amount in your palm and briskly rub hands together until dry.

Inactive Ingredients:

Water,Carbomer 940,Triethanolamine,Glycerin,Aloe Barbadensis Leaf Juice,Vitamin E